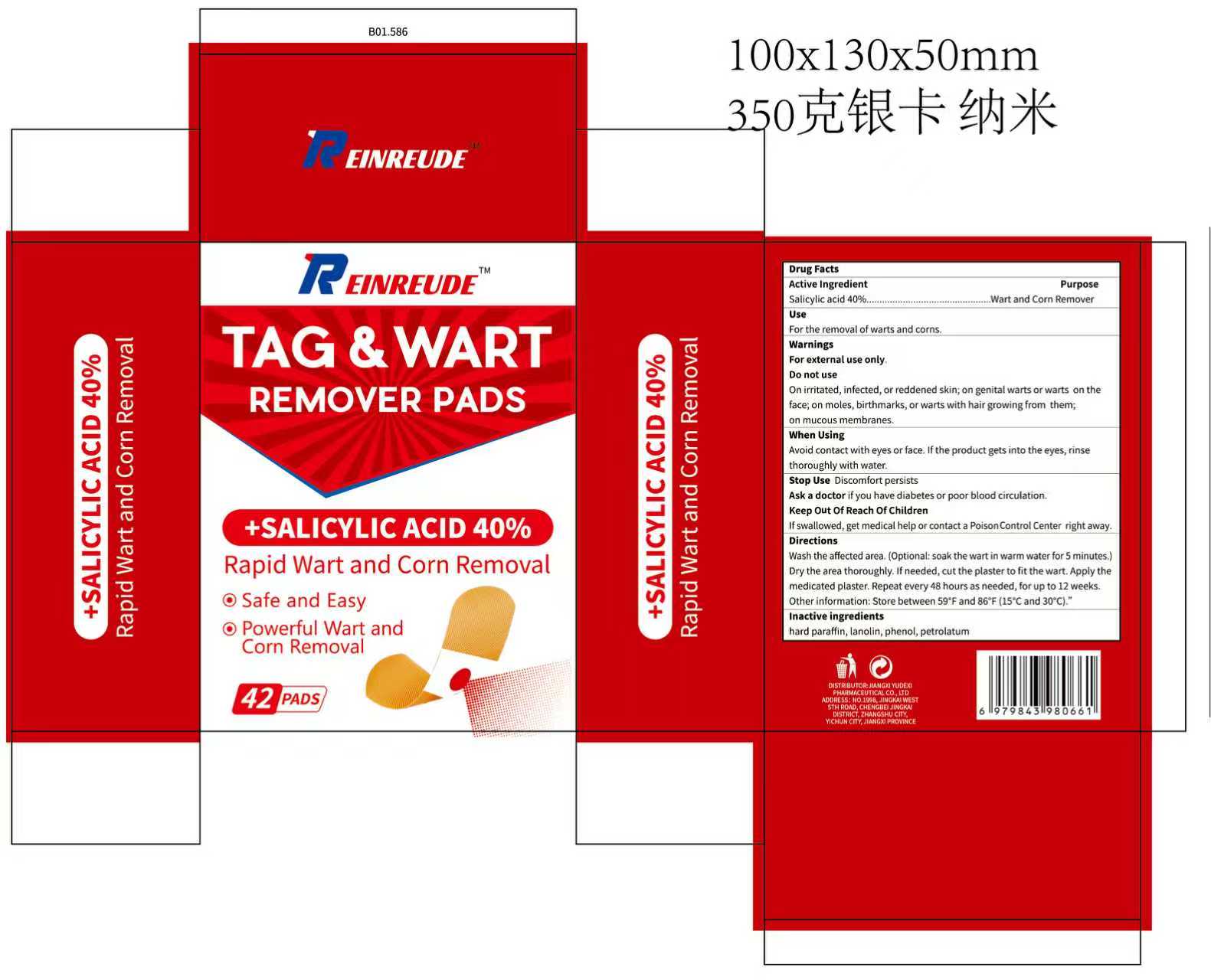 DRUG LABEL: REINREUDE TAG WART REMOVER
NDC: 85248-075 | Form: PATCH
Manufacturer: Jiangxi Yudexi Pharmaceutical Co., LTD
Category: otc | Type: HUMAN OTC DRUG LABEL
Date: 20260209

ACTIVE INGREDIENTS: SALICYLIC ACID 40 g/100 1
INACTIVE INGREDIENTS: PHENOL; LANOLIN; PETROLATUM; PARAFFIN

85248-075

Active Ingredient

Salicylic acid 40%

Purpose

Wart and Corn Remover

Use

For the removal of warts and corns.

Warnings

For external use only.

Do not use

On irritated,infected, or reddened skin; on genital warts or warts on the face; on moles, birthmarks, or warts with hair growing from them;on mucous mempranes.

When Using

Avoid contact with eyes or face. lf the product gets into the eyes, rinse thoroughly with water.

Stop Use

Discomfort persists

Ask Doctor

Ask a doctor if you have diabetes or poor blood circulation.

Keep Oot Of Reach Of Children

If swallowed, get medical help or contact a Poison control Center right away.

Directions

Wash the affected area. (Optional: soak the wart in warm water for 5 minutes.Dry the area thoroughly. lf needed, cut the plaster to fit the wart. Apply the medicated plaster. Repeat every 48 hours as needed, for up to 12 weeks.Other information: Store between 59°F and 86°F(15°C and 30°C).

Inactive ingredients

hard paraffin,lanolin,phenol, petrolatum